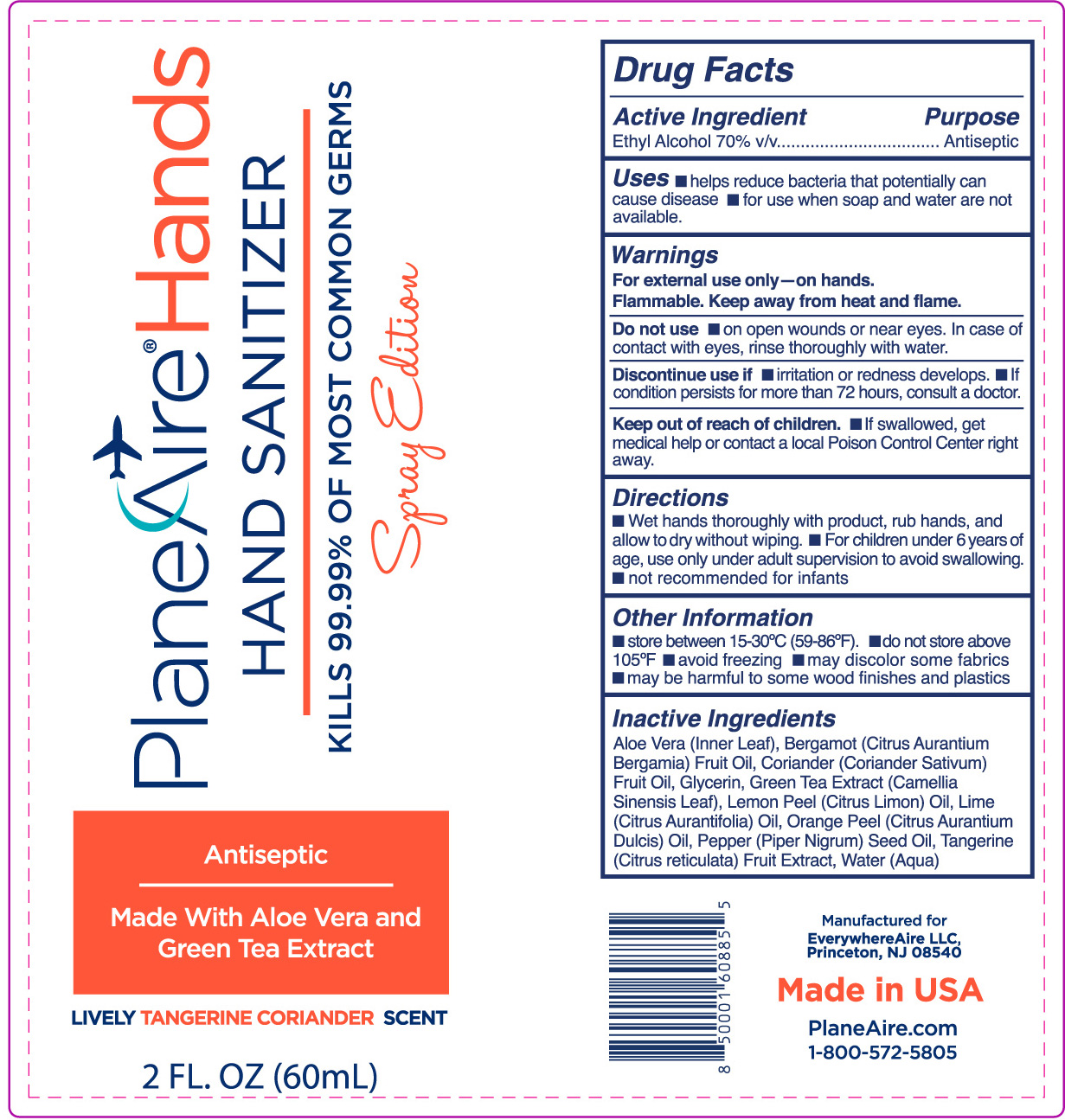 DRUG LABEL: PlaneAire Hands
NDC: 80335-117 | Form: SPRAY
Manufacturer: EverywhereAire LLc
Category: otc | Type: HUMAN OTC DRUG LABEL
Date: 20231220

ACTIVE INGREDIENTS: ALCOHOL 70 mL/100 mL
INACTIVE INGREDIENTS: LIME OIL; CORIANDER OIL; ALOE VERA LEAF POLYSACCHARIDES; TANGERINE; LEMON OIL; BERGAMOT OIL; GREEN TEA LEAF; WATER; BLACK PEPPER OIL; GLYCERIN; ORANGE OIL

PlaneAire Hands spray tangerine coriander with aloe vera, green tea, lemon, lime, bergamot , and pepper oils

Active Ingredient

Ethyl alcohol 70% V/V

Purpose

Antiseptic

Uses

helps reduce bacteria that potentially can cause disease

for use when soap and water are not available

Warnings

For external use only- on hands

Flammable. Keep away from heat and flame

Do not use

on open wounds or near eyes. In case of contact with eyes, rinse thoroughly with water

Discontinue use if

- irritation or redness develops
- If condtion persists for more than 72 hiurs, consult a doctor

Keep out of reach of children

- If swallowed, get medical help or contact a local Poison Control Center right away

Directions

- Wet hands thoroughly with product, rub hands, and allow to dry without wiping
- For children under 6 years of age, use only under adult supervision to avoid swallowing
- not recommended for infants

Other Information

- store between 15-30 C (59-86 F)
- do not store above 105 F
- avoid freezing
- may discolor some fabrics
- may be harmful to some wood finishes and plastics

Inactive Ingredients

Aloe Vera (Inner Leaf), Bergamot (Citrus Aurantium Bergamia) Fruit Oil, Coriander (Coriander Sativum) Fruit OIl, Glycerin, Green Tea Extract (Camellia Sinensis Leaf), Lemon Peel (Citrus Limon) Oil, Orange Peel (Citrus Aurantium Dulcis) Oil, Pepper (Piper Nigrum) Seed Oil, Tangerine (Citrus reticulata) Fruit Extract, Water (Aqua)

Dosage and Administration Indications and Usage- Uses:

Section title changed

Section text reformatted to single line

reassigned section heading and number, bullets remioved